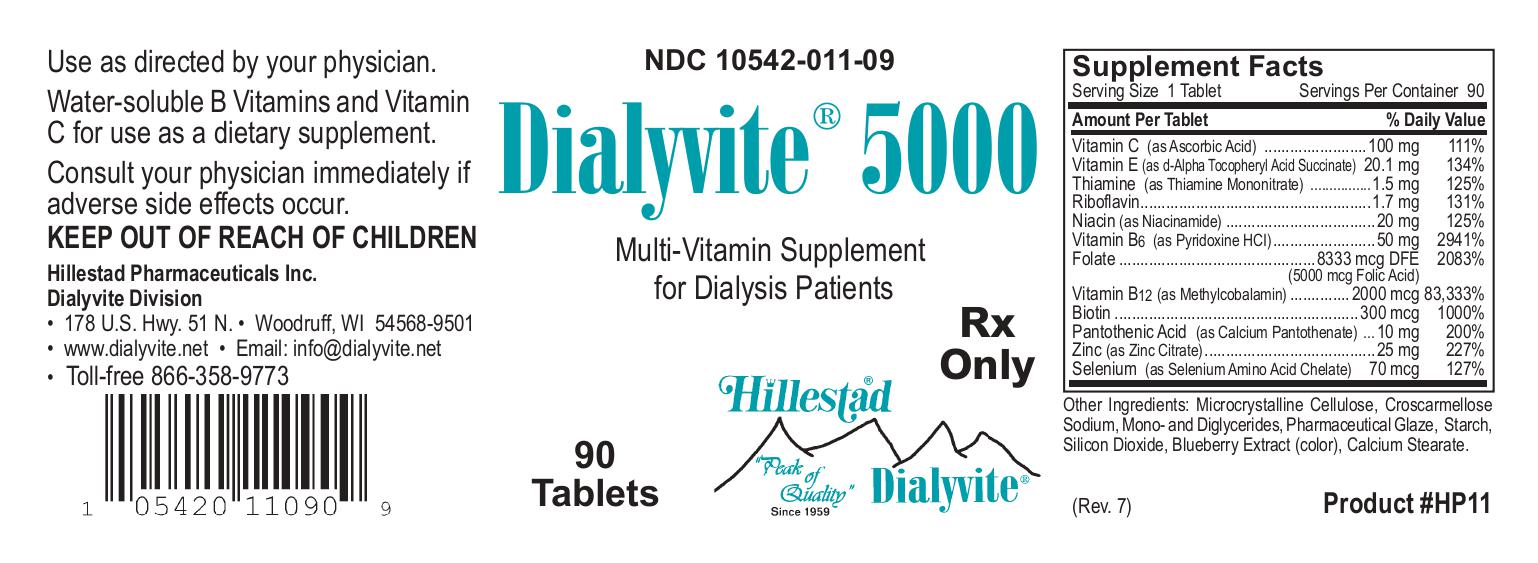 DRUG LABEL: Dialyvite 5000
NDC: 10542-011 | Form: TABLET, COATED
Manufacturer: Hillestad Pharmaceuticals USA
Category: prescription | Type: HUMAN PRESCRIPTION DRUG LABEL
Date: 20260127

ACTIVE INGREDIENTS: Ascorbic Acid 100 mg/1 1; Thiamine Mononitrate 1.5 mg/1 1; Riboflavin 1.7 mg/1 1; Niacinamide 20 mg/1 1; Pyridoxine Hydrochloride 50 mg/1 1; Folic Acid 5 mg/1 1; Cobalamin 2 mg/1 1; Biotin 300 ug/1 1; Calcium Pantothenate 10 mg/1 1; Zinc Citrate 25 mg/1 1; .alpha.-tocopherol succinate, d-  30 [iU]/1 1; Selenocysteine 70 ug/1 1
INACTIVE INGREDIENTS: Microcrystalline Cellulose; Croscarmellose Sodium; Glyceryl Monostearate; Shellac; Starch, Corn; Silicon Dioxide; Blueberry; Calcium Stearate

Dialyvite 5000

DESCRIPTION

Dialyvite 5000 is a prescription folic acid supplement with additional nutrients for kidney dialysis patients. Dialyvite 5000 is a small, round, purple, coated tablet, with debossed "H" on one side.

Each tablet contains:

Folic Acid.....5 mg

Vitamin E (d-alpha Tocopheryl Acid Succinate).....30 IU

Vitamin C (Ascorbic Acid).....100 mg

Thiamine (Thiamine Mononitrate).....1.5 mg

Riboflavin.....1.7 mg

Niacinamide.....20 mg

Vitamin B6 (Pyridoxine HCl).....50 mg

Vitamin B12 (Methylcobalamin).....2 mg

Biotin.....300 mcg

Pantothenic Acid (Calcium Pantothenate).....10 mg

Zinc (Zinc Citrate).....25 mg

Selenium (Selenium Amino Acid Chelate).....70 mcg

Inactive ingredients:

Microcrystalline Cellulose, Croscarmellose Sodium, Mono-and Diglycerides, Pharmaceutical Glaze, Starch, Silicon Dioxide, Blueberry Extract (color), Calcium Stearate.

INDICATIONS AND USAGE

Dialyvite 5000 is a prescription folic acid supplement with additional nutrients indicated for use in improving the nutritional status of renal dialysis patients.

CONTRAINDICATIONS

This product is contraindicated in patients with known hypersensitivity to any of the ingredients.

PRECAUTIONS

Folic acid supplementation may obscure pernicious anemia, in that hematologic remission can occur while neurological manifestations progress.

Keep out of reach of children.

ADVERSE REACTIONS

Allergic sensitizations have been reported following oral administration of folic acid.

Consult your physician immediately if adverse side effects occur.

DOSAGE AND ADMINISTRATION

Take one tablet per day or use as directed by your physician, orally.

PRINCIPAL DISPLAY PANEL

NDC 10542-011-09

Dialyvite 5000

Multivitamin Supplement for Dialysis Patients

90 Tablets